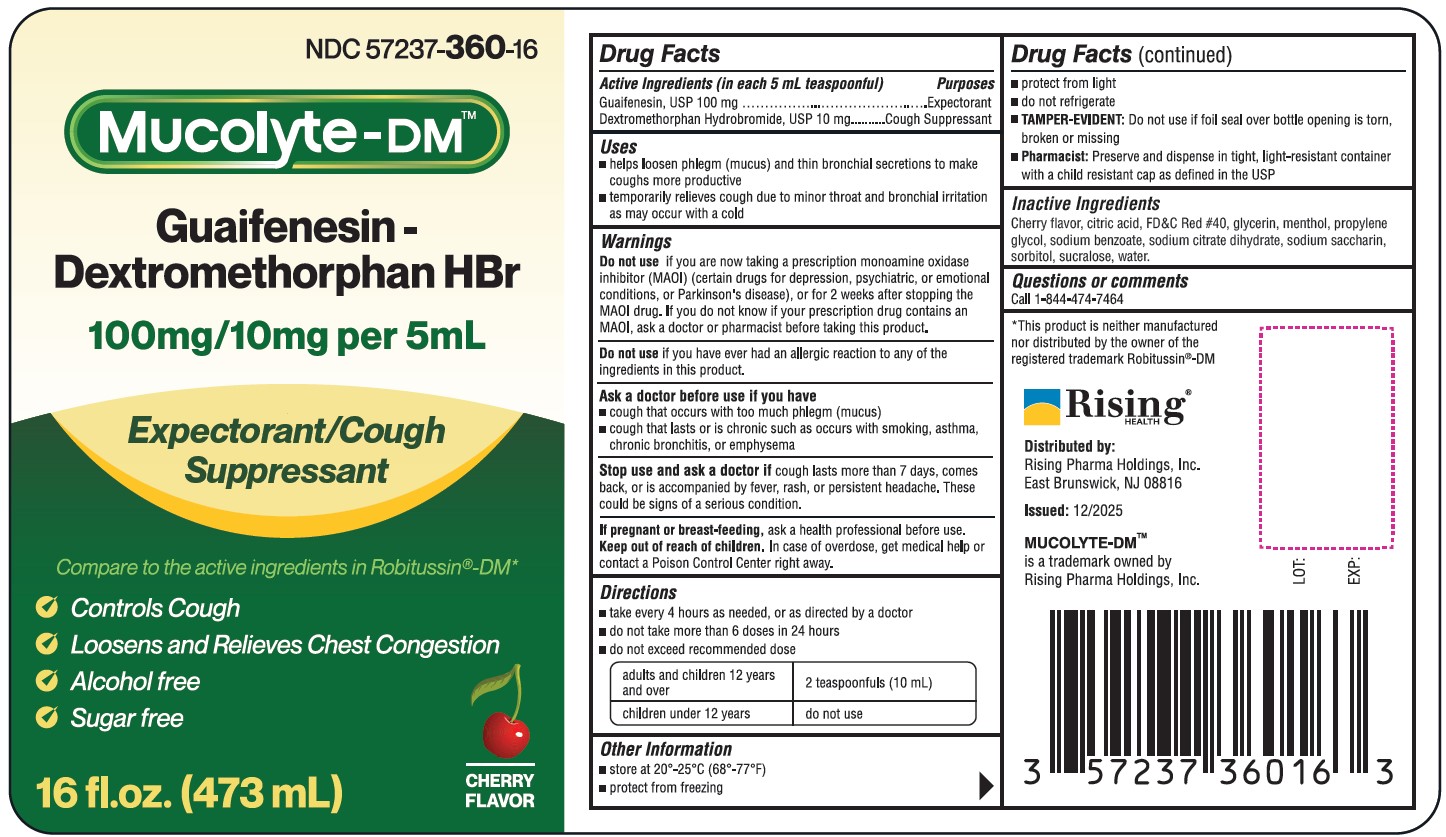 DRUG LABEL: Mucolyte
NDC: 57237-360 | Form: LIQUID
Manufacturer: Rising Pharma Holdings, Inc.
Category: otc | Type: HUMAN OTC DRUG LABEL
Date: 20251208

ACTIVE INGREDIENTS: GUAIFENESIN 100 mg/5 mL; DEXTROMETHORPHAN HYDROBROMIDE 10 mg/5 mL
INACTIVE INGREDIENTS: CITRIC ACID; FD&C RED NO. 40; GLYCERIN; MENTHOL; PROPYLENE GLYCOL; SODIUM BENZOATE; SODIUM CITRATE, UNSPECIFIED FORM; SODIUM SACCHARIN; SORBITOL; SUCRALOSE; WATER

Mucolyte-DM
Guaifenesin-Dextromethorphan HBr

Drug Facts

Active Ingredients (in each 5 mL teaspoonful)

Guaifenesin, USP 100 mg

Dextromethorphan Hydrobromide, USP 10 mg

Purposes

Expectorant

Cough Suppressant

Uses

- helps loosen phlegm (mucus) and thin bronchial secretions to make coughs more productive
- temporarily relieves cough due to minor throat and bronchial irritation as may occur with a cold

Warnings

Do not use if you are now taking a prescription monoamine oxidase inhibitor (MAOI) (certain drugs for depression, psychiatric or emotional conditions, or Parkinson’s disease), or for 2 weeks after stopping the MAOI drug. If you do not know if your prescription drug contains an MAOI, ask a doctor or pharmacist before taking this product.

Do not use if you have ever had an allergic reaction to any of the ingredients in this product.

Ask a doctor before use if you have

- cough that occurs with too much phlegm (mucus)
- cough that lasts or is chronic such as occurs with smoking, asthma, chronic bronchitis or emphysema

Stop use and ask a doctor if cough lasts more than 7 days, comes back, or is accompanied by fever, rash, or persistent headache. These could be signs of a serious condition.

PREGNANCY OR BREAST FEEDING

If pregnant or breast-feeding, ask a health professional before use.

Keep out of reach of children. In case of overdose, get medical help or contact a Poison Control Center right away.

Directions

- take every 4 hours as needed, or as directed by a doctor
- do not take more than 6 doses in 24 hours
- do not exceed recommended dose

adults and children 12 years and over | 2 teaspoonfuls (10 mL)
children under 12 years | do not use

Other Information

- store at 20°-25°C (68°-77°F)
- protect from freezing
- protect from light
- do not refrigerate
- TAMPER-EVIDENT: Do not use if foil seal over bottle is torn, broken or missing
- Pharmacist: Preserve and dispense in tight, light-resistant container with a child resistant cap as defined in the USP

Inactive Ingredients

Cherry flavor, citric acid, FD&C Red #40, glycerin, menthol, propylene glycol, sodium benzoate, sodium citrate dihydrate, sodium saccharin, sorbitol, sucralose, water.

Questions or comments

Call 1-844-474-7464

OTHER SAFETY INFORMATION

*This product is neither manufactured nor distributed by the owner of the registered trademark Robitussin®-DM

MUCOLYTE-DMTM is a trademark owned by Rising Pharma Holdings, Inc.

Distributed by:
Rising Pharma Holdings, Inc.
East Brunswick, NJ 08816